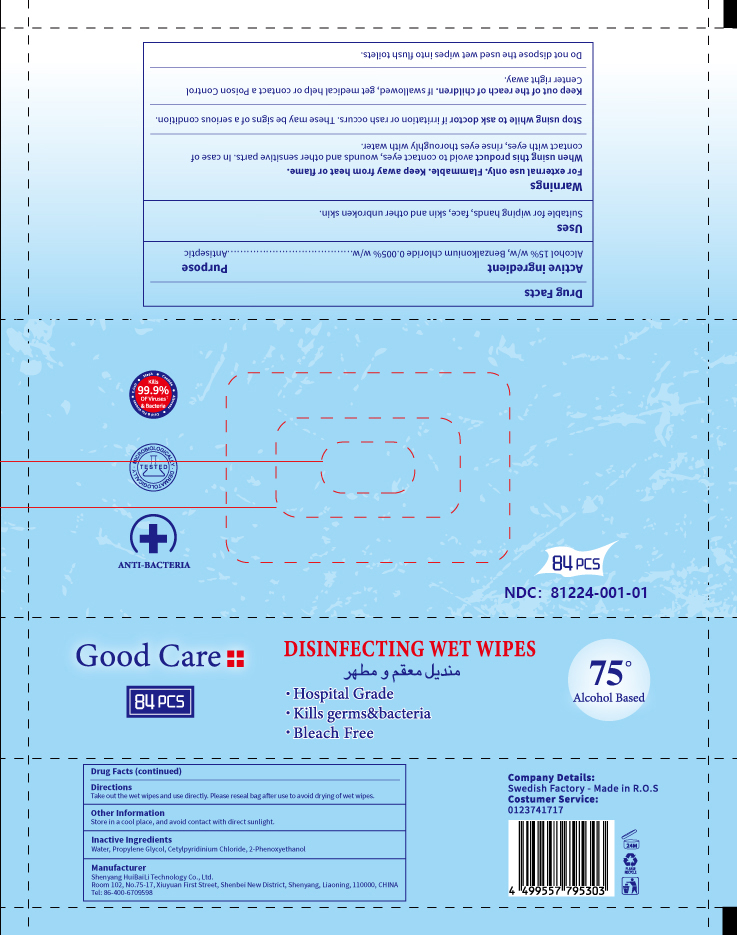 DRUG LABEL: HuiBaiLi DISINFECTING WET WIPES
NDC: 81224-001 | Form: CLOTH
Manufacturer: Shenyang Huibaili Technology Co., Ltd.
Category: otc | Type: HUMAN OTC DRUG LABEL
Date: 20201220

ACTIVE INGREDIENTS: BENZALKONIUM CHLORIDE 0.0002416 g/1 1; ALCOHOL 0.7249 g/1 1
INACTIVE INGREDIENTS: PROPYLENE GLYCOL; PHENOXYETHANOL; WATER; CETYLPYRIDINIUM CHLORIDE ANHYDROUS

HuiBaiLi DISINFECTING WET WIPES

Active ingredient

Alcohol 15% w/w, Benzalkonium chloride 0.005% w/w

Purpose

Antiseptic

Uses

Suitable for wiping hands, face, skin and other unbroken skin.

Warnings

For external use only. Flammable. Keep away from heat or flame.

When using this product avoid to contact eyes, wounds and other sensitive parts. In case of contact with eyes, rinse eyes thoroughly with water.

Stop using while to ask doctor if irritation or rash occurs. These may be signs of a serious condition.

Keep out of the reach of children. If swallowed, get medical help or contact a Poison Control Center right away.

Do not dispose the used wet wipes into flush toilets.

When using this product avoid to contact eyes, wounds and other sensitive parts. In case of contact with eyes, rinse eyes thoroughly with water.

STOP USE

Stop using while to ask doctor if irritation or rash occurs. These may be signs of a serious condition.

KEEP OUT OF REACH OF CHILDREN

Keep out of the reach of children. If swallowed, get medical help or contact a Poison Control Center right away.

Directions

Take out the wet wipes and use directly. Please reseal bag after use to avoid drying of wet wipes.

Other Information

Store in a cool place, and avoid contact with direct sunlight.

Inactive Ingredients

Water, Propylene Glycol, Cetylpyridinium Chloride, 2-Phenoxyethanol

PACKAGE LABEL

84PCS, NDC: 81224-001-01